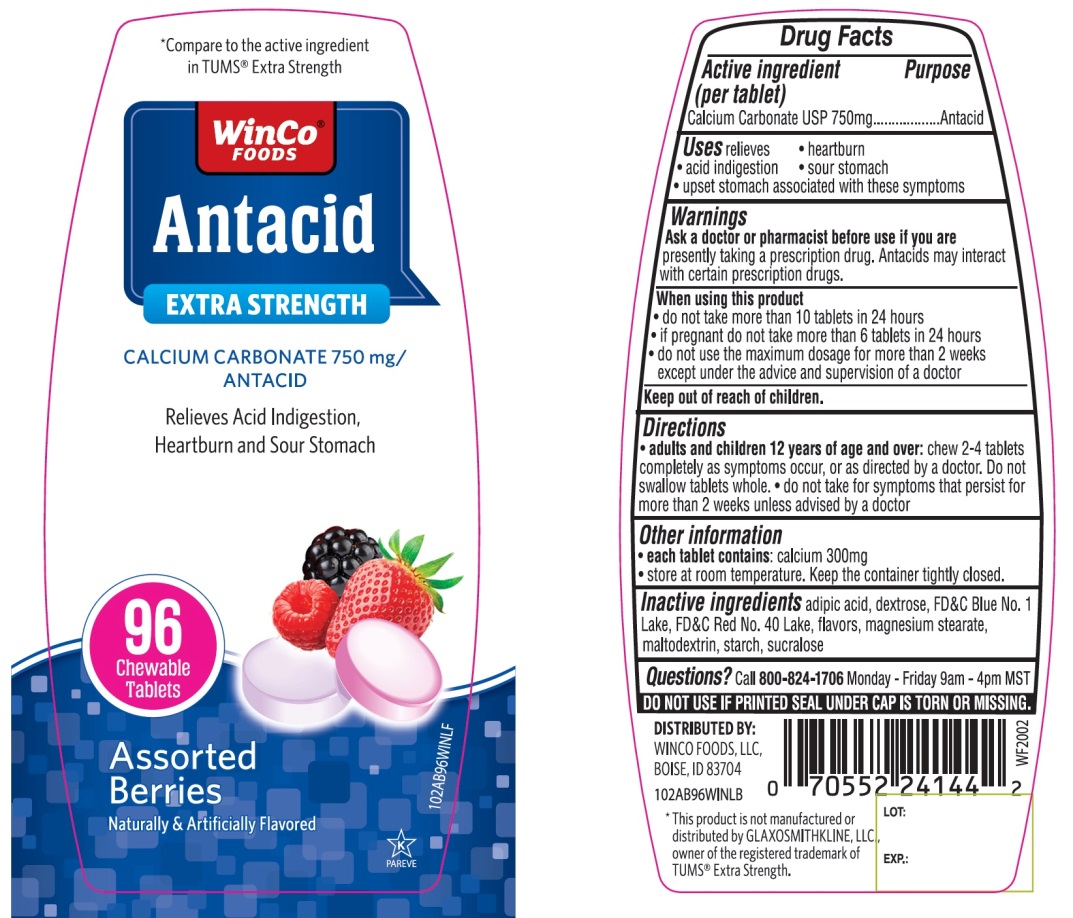 DRUG LABEL: WinCo FOODS Antacid

NDC: 67091-359 | Form: TABLET, CHEWABLE
Manufacturer: WINCO FOODS, LLC
Category: otc | Type: HUMAN OTC DRUG LABEL
Date: 20251202

ACTIVE INGREDIENTS: CALCIUM CARBONATE 750 mg/1 1
INACTIVE INGREDIENTS: ADIPIC ACID; DEXTROSE, UNSPECIFIED FORM; FD&C BLUE NO. 1; FD&C RED NO. 40; MAGNESIUM STEARATE; MALTODEXTRIN; STARCH, CORN; SUCRALOSE

WinCo FOODS Extra Strength Calcium Carbonate Assorted Berries 96 Chewable Tablets

Active ingredient (per tablet)

Calcium Carbonate USP 750mg

Purpose

Antacid

Uses

relieves

- heartburn
- acid indigestion
- sour stomach
- upset stomach associated with these symptoms

Warnings

Ask a doctor or pharmacist before use if you arepresently taking a prescription drug. Antacids may interact with certain prescription drugs.

When using this product

- do not take more than 10 tablets in 24 hours
- If pregnant do not take more than 6 tablets in 24 hours
- do not use the maximum dosage for more than 2 weeks except under the advice and supervision of a doctor

Directions

- adults and children 12 years of age and over:chew 2-4 tablets as symptoms occur or as directed by a doctor. Do not swallow tablets whole.
- do not take for symptoms that persist for more than 2 weeks unless advised by a doctor

Other Information

- each tablet contains:calcium 300mg
- store at room temperature. Keep the container tightly closed.

Inactive ingredients

adipic acid, dextrose, FD&C Blue No. 1 Lake, FD&C Red No. 40 Lake, flavors, magnesium stearate, maltodextrin, starch, sucralose.

Questions?

1-800-824-1706

SAFETY SEALED: DO NOT USE IF PRINTED SEAL UNDER CAP IS TORN OR MISSING

Package/Label Principal Display Panel

WinCo®FOODS

NDC# 67091-359-96

Compare to the active ingredient in Extra Strength Tums®

Antacid

EXTRA STRENGTH

CALCIUM CARBONATE 750 mg/ANTACID

Assorted Berries Flavor

Naturally & Artificially Flavored

Relieves Acid Indigestion, Heartburn and Sour Stomach

96 CHEWABLE TABLETS

K PAREVE

GLUTEN-FREE

DISTRIBUTED. BY:

WINCO FOODS, LLC

BOISE, ID 83704

*This product is not manufactured or distributed by GLAXOSMITHKLINE LLC, owner of the registered trademark of TUMS®Extra Strength